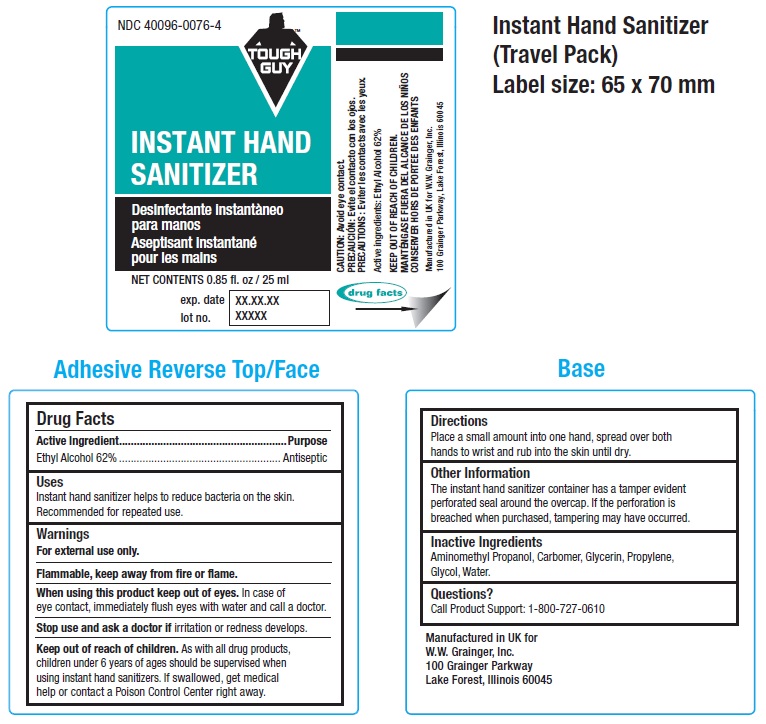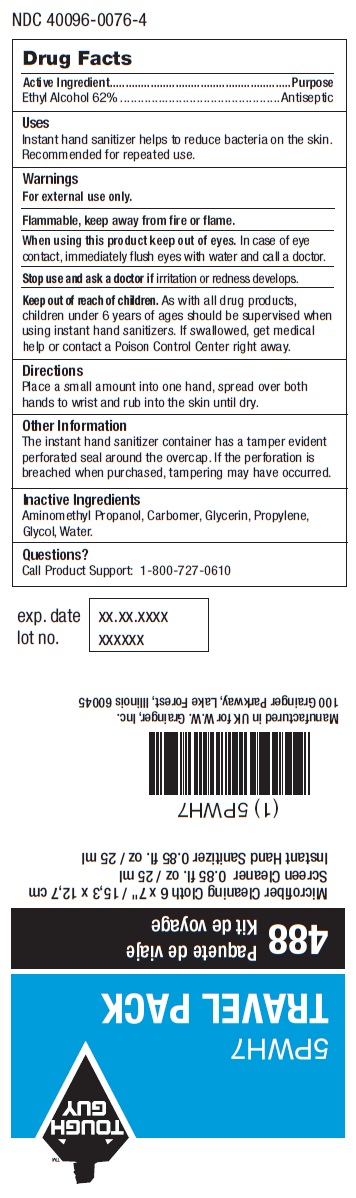 DRUG LABEL: TOUGH GUY INSTANT HAND SANITIZER
NDC: 40096-0076 | Form: LIQUID
Manufacturer: W.W. Grainger, Inc.
Category: otc | Type: HUMAN OTC DRUG LABEL
Date: 20101101

ACTIVE INGREDIENTS: ALCOHOL 62 mL/100 mL
INACTIVE INGREDIENTS: AMINOMETHYLPROPANOL; GLYCERIN; PROPYLENE GLYCOL; WATER

TOUGH GUY INSTANT HAND SANITIZER

DRUG FACTS

ACTIVE INGREDIENT PURPOSE

ETHYL ALCOHOL 62% ANTISEPTIC

PURPOSE
ANTISEPTIC

USES

Instant hand sanitizer helps to reduce bacteria on the skin. Recommended for repeated use.

WARNINGS
For external use only.

flammable, keep away from fire or flame

When using this product keep out of eyes. In case of eye contact, immediately flush eyes with water and call a doctor.

Stop use and ask a doctor if irritation or redness develops.

Keep out of reach of children. As with all drug products, children under 6 years of ages should be supervised when using instant hand sanitizers. If swallowed, get medical help or contact a Poison Control Center right away.

DIRECTIONS

Place a small amount into one hand, spread over both hands to wrist and rub into the skin until dry.

OTHER INFORMATION

The instant hand sanitizer container has a tamper evident perforated seal round the overcap. If the perforation is breached when purchased, tampering may have occurred

INACTIVE INGREDIENTS

Aminomethyl propanol, carbomer, glycrin, propylene glycol, water.

Questions?

Call product support 1-800-727-0610

Manufactured in UK for

W.W. Grainger, Inc.

100 Grainger Parkway

Lake Forest Illinois 60045

PACKAGE LABEL

Ndc 40096-0076-4
TOUGH GUY
INSTANT HAND SANITIZER
DISINFECTANTE INSTANTANEO PARA MANOS
ASEPTISANT INSTANTANE POUR LES MAINS
NET CONTENTS 0.85 FL OZ / 25ML
EXP DATE
LOT NO.
CAUTION: AVOID EYE CONTACT
PRECAUCION: EVITE EL CONTACTO CON LOS OJOS
PRECAUTIONS: EVITER LES CONTACTS AVEC LES YEUX
ACTIVE INGREDIENTS: ETHYL ALCOHOL 62%
KEEP OUT OF REACH OF CHILDREN
MANTENGASE PUERA DEL ALCANCE DE LOS NINOS
CONSERVOR HORS DE PORTEE DES ENFANTS
MANUFACTURED IN UK FOR W.W. GRAINGER, INC.
100 GRAINGER PARKWAY, LAKE FOREST ILLINOIS 60045